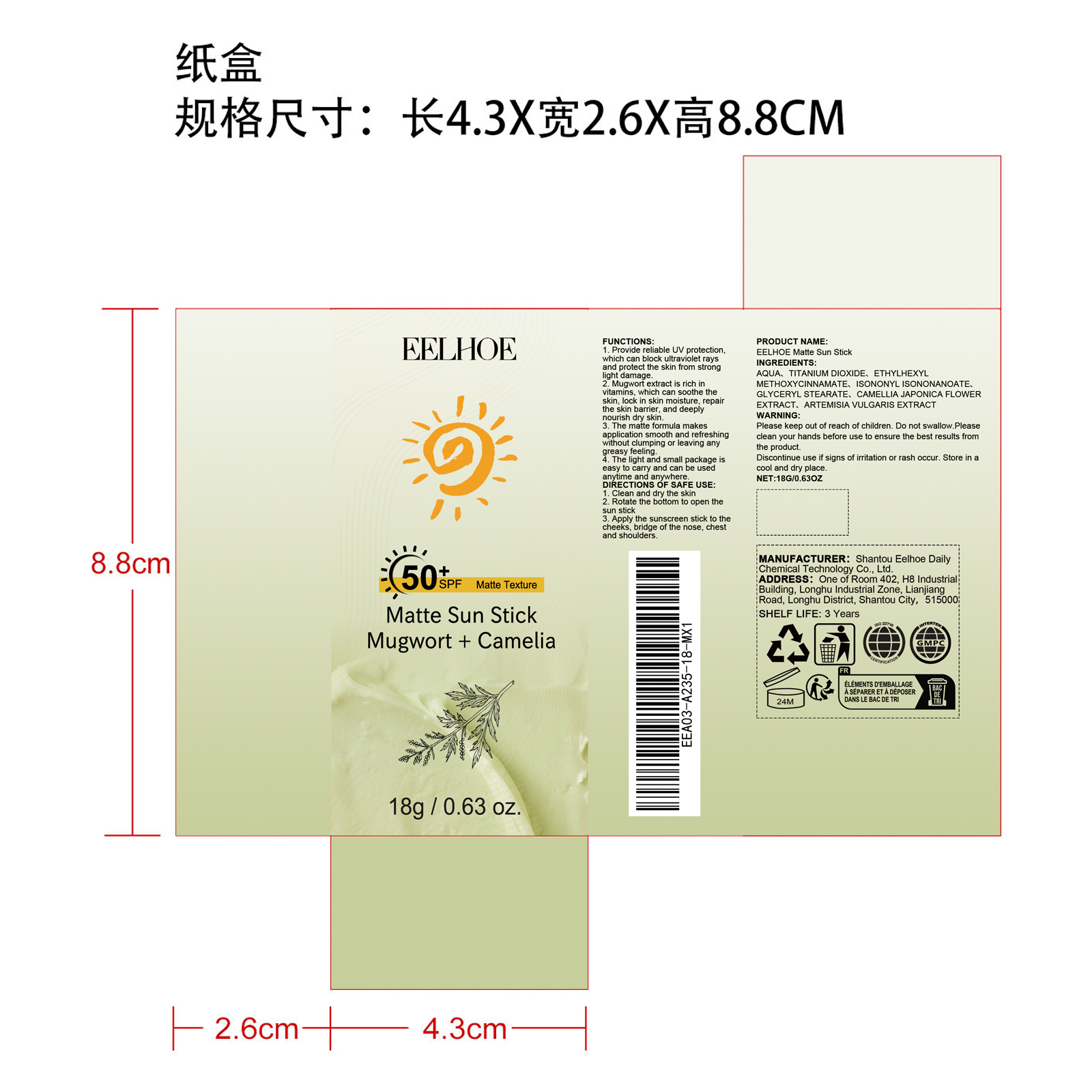 DRUG LABEL: EELHOE Matte Sun Stick
NDC: 85064-017 | Form: CREAM
Manufacturer: Shantou Eelhoe Daily Chemical Technology Co., Ltd.
Category: otc | Type: HUMAN OTC DRUG LABEL
Date: 20251127

ACTIVE INGREDIENTS: CAMELLIA JAPONICA FLOWER 0.054 mg/18 mg; ARTEMISIA VULGARIS ROOT 0.0036 mg/18 mg
INACTIVE INGREDIENTS: ISONONYL ISONONANOATE 0.72 mg/18 mg; AQUA 14.6124 mg/18 mg; GLYCERYL STEARATE 0.27 mg/18 mg; ETHYLHEXYL METHOXYCINNAMATE 0.9 mg/18 mg; TITANIUM DIOXIDE 1.44 mg/18 mg

Active Ingredient(s)

CAMELLIA JAPONICA FLOWER EXTRACT、ARTEMISIA VULGARIS EXTRACT

Purpose

1. Provide reliable UV protection, which can block ultraviolet rays and protect the skin from strong light damage.

2. Mugwort extract is rich in vitamins, which can soothe the skin, lock in skin moisture, repair the skin barrier, and deeply nourish dry skin.

3. The matte formula makes application smooth and refreshing without clumping or leaving any greasy feeling.

4. The light and small package is easy to carry and can be used anytime and anywhere.

Use

1. Clean and dry the skin

2. Rotate the bottom to open the sun stick

3. Apply the sunscreen stick to the cheeks, bridge of the nose, chest and shoulders.

Warning

Please keep out of reach of children. Do not swallow.Please clean your hands before use to ensure the best results from the product. Discontinue use if signs of irritation or rash occur. Store in a cool and dry place.

DO NOT USE

Discontinue use if signs of irritation or rash occur.

STOP USE

Discontinue use if signs of irritation or rash occur.

KEEP OUT OF REACH OF CHILDREN

Please keep out of reach of children. Do not swallow.

STORAGE AND HANDLING

Store in a cool and dry place.

INACTIVE INGREDIENT

AQUA、TITANIUM DIOXIDE、ETHYLHEXYL METHOXYCINNAMATE、ISONONYL ISONONANOATE、GLYCERYL STEARATE

INDICATIONS AND USAGE

1. Clean and dry the skin

2. Rotate the bottom to open the sun stick

3. Apply the sunscreen stick to the cheeks, bridge of the nose, chest and shoulders.

DOSAGE AND ADMINISTRATION

1. Clean and dry the skin

2. Rotate the bottom to open the sun stick

3. Apply the sunscreen stick to the cheeks, bridge of the nose, chest and shoulders.